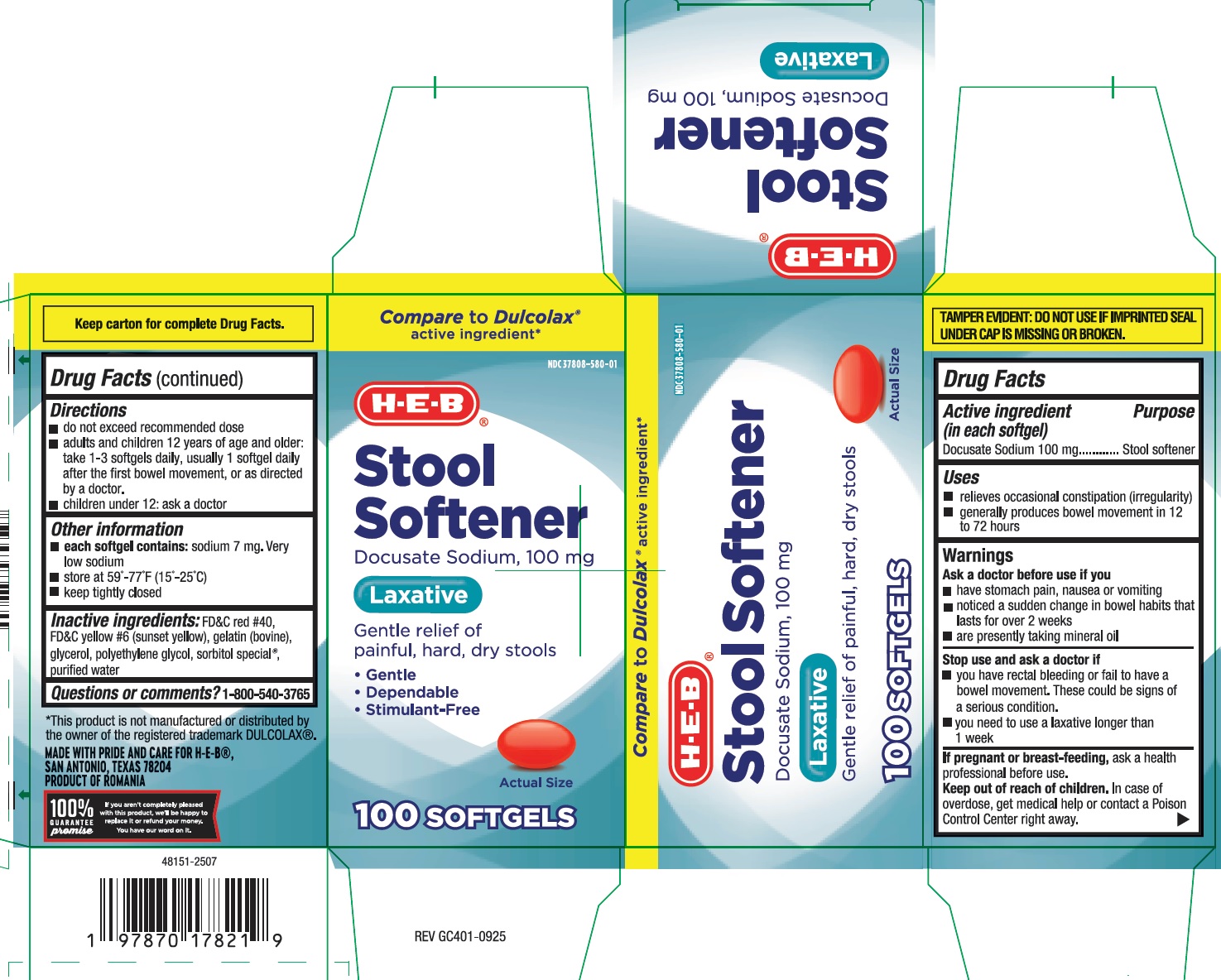 DRUG LABEL: Stool Softener
NDC: 37808-580 | Form: CAPSULE, LIQUID FILLED
Manufacturer: HEB
Category: otc | Type: HUMAN OTC DRUG LABEL
Date: 20251208

ACTIVE INGREDIENTS: DOCUSATE SODIUM 100 mg/1 1
INACTIVE INGREDIENTS: GELATIN; GLYCERIN; POLYETHYLENE GLYCOL 400; SORBITOL; WATER; FD&C YELLOW NO. 6; FD&C RED NO. 40

heb 401

Active ingredient (in each softgel)

Docusate Sodium 100 mg

Purpose

Stool Softener

Uses

- relieves occasional constipation (irregularity)

- generally produces bowel movement in 12 to 72 hours

Warnings

Ask a doctor before use if you

• have stomach pain, nausea or vomiting

• have a sudden change in bowel habits that persists over a period of 2 weeks

• are presently taking mineral oil

Stop use and ask a doctor if

• you need to use a laxative longer than 1 week

• you have rectal bleeding or fail to have a bowel movement. These

could be signs of a serious condition.

If pregnant or breast-feeding, ask a health professional before use.

Keep out of reach of children. In case of overdose, get medical help or contact a Poison Control Center right away.

Directions

- do not exceed recommended dose
- adults and children 12 years and older: take 1-3 softgels daily, usually 1 softgel daily after the first bowel movement, or as directed by a doctor.
- children under 12: ask a doctor

Other information

• each softgel contains: sodium 7 mg. Very low sodium
• store at 59°-77°F (15°-25°C)
• keep tightly closed

Inactive ingredients

FD&C red #40, FD&C yellow #6 (sunset yellow), gelatin (bovine), glycerol, polyethylene glycol, sorbitol special, purified water.

Questions or comments?

1-800-540-3765